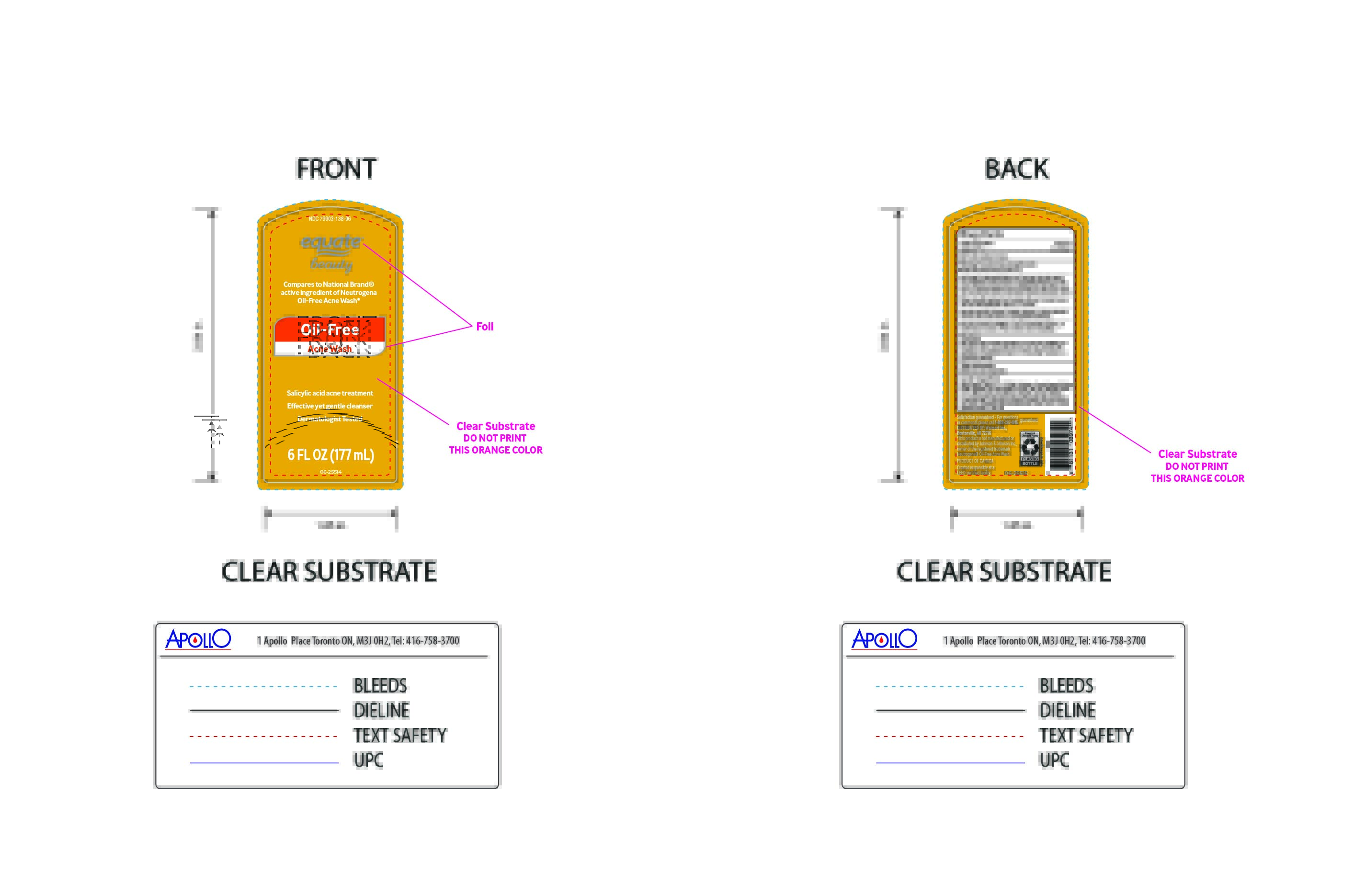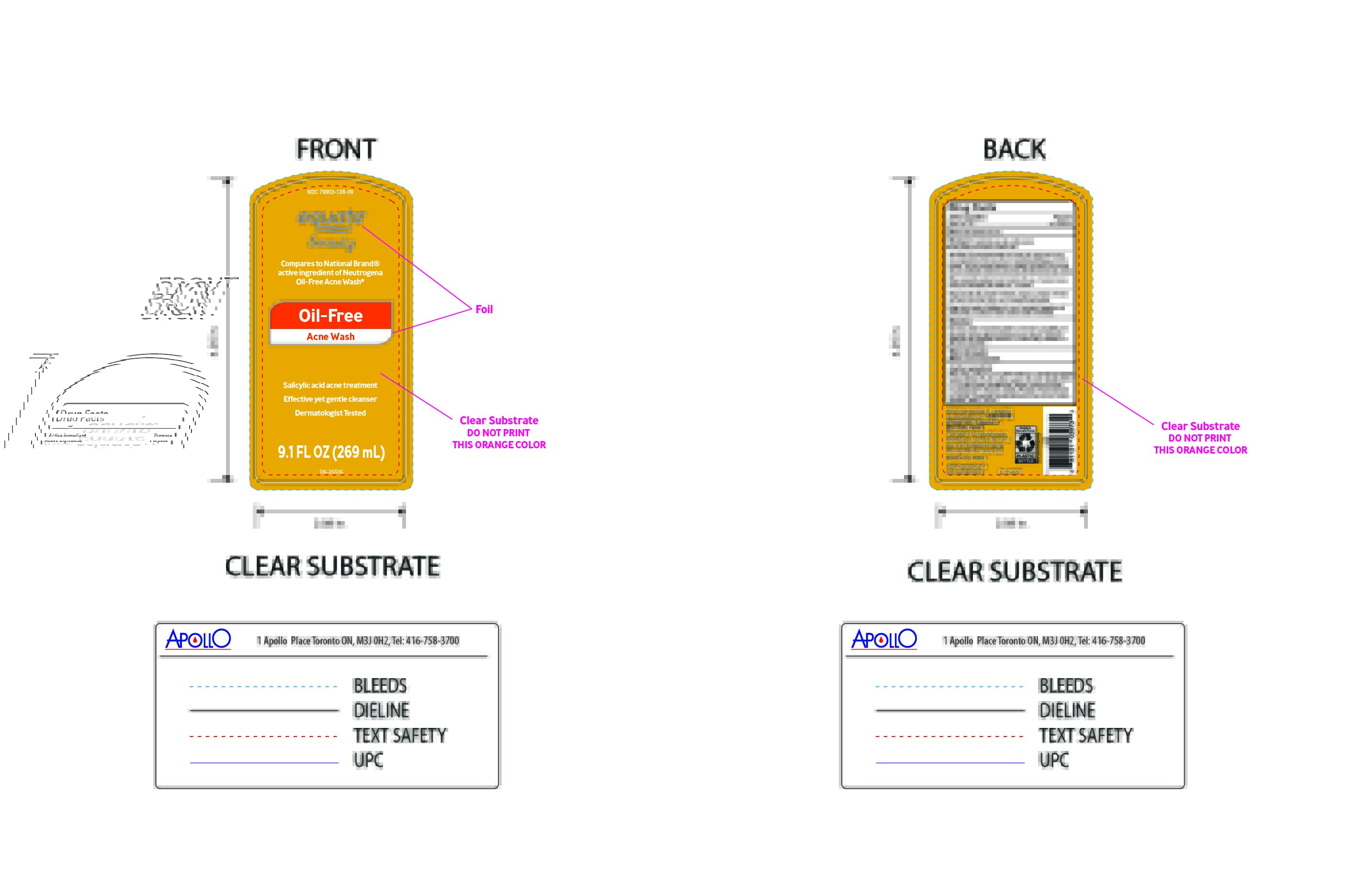 DRUG LABEL: Equate Beauty
NDC: 79903-138 | Form: SOAP
Manufacturer: WALMART INC.
Category: otc | Type: HUMAN OTC DRUG LABEL
Date: 20250103

ACTIVE INGREDIENTS: SALICYLIC ACID 2000 mg/100 mL
INACTIVE INGREDIENTS: FD&C RED NO. 40; FRAGRANCE CLEAN ORC0600327; WATER; MATRICARIA CHAMOMILLA FLOWERING TOP; BASIC YELLOW 5; EDETATE DISODIUM; COCAMIDOPROPYL PG-DIMONIUM CHLORIDE PHOSPHATE; ALOE VERA LEAF; SODIUM HYDROXIDE; PEG-80 SORBITAN LAURATE; C12-15 ALKYL LACTATE; BENZALKONIUM CHLORIDE; CITRIC ACID MONOHYDRATE; SODIUM C14-16 OLEFIN SULFONATE; COCAMIDOPROPYL BETAINE; SODIUM CHLORIDE

Oil Free Acne Wash

Active Ingredient

Salicylic Acid

PURPOSE

Acne treatment

Indication and Usage

To be used to treat pimples (acne)..

WARNINGS

For external use only:

- Flammable
- keep away from source of heat or Fire

Ask doctor or pharmacist before use if you are using other topical acne medications at the same time or immediately following use of
this product. This may increase dryness or irritation of the skin. If this occurs, only one medication should be used unless otherwise directed by a doctor.

When using this product avoid contact with eyes. If contact occurs, rinse eyes thoroughly with water for 15 minutes.

Stop use and ask a doctor if irritation, dryness or redness develops and lasts. Ask doctor before use if pregnant/breastfeeding.

Keep out of reach of children. In case of accidental ingestion, get medical help or contact a Poison Control Center immediately.

Directions

New Users: Apply to small area before use to test for sensitivity. If no discomfort occurs, apply to affected area and rinse off. Start with one application and gradually increase to 2-3 times daily if needed or as directed by physician.

Other Information

- Store at room temperature.

Inactive ingredients

Water (Aqua), Soduum C14-16 Olefin Sulfonate, Cocamidopropyl Betaine, Sodium Chloride, PEG-80 Sorbitan Laurate, Citric Acid, , Disodium EDTA, C12-15 Alkyl Lactate, Benzolkonium Chloride, Fragrance (Parfum), Cocamidopropyl PG-Dimonium Chloride Phosphate, Aloe Barbadensis, Leaf Extract, Chamomilla Recutita(Matricaria) Flower Extract, Sodium Hydroxide , Yellow 5, Red 40